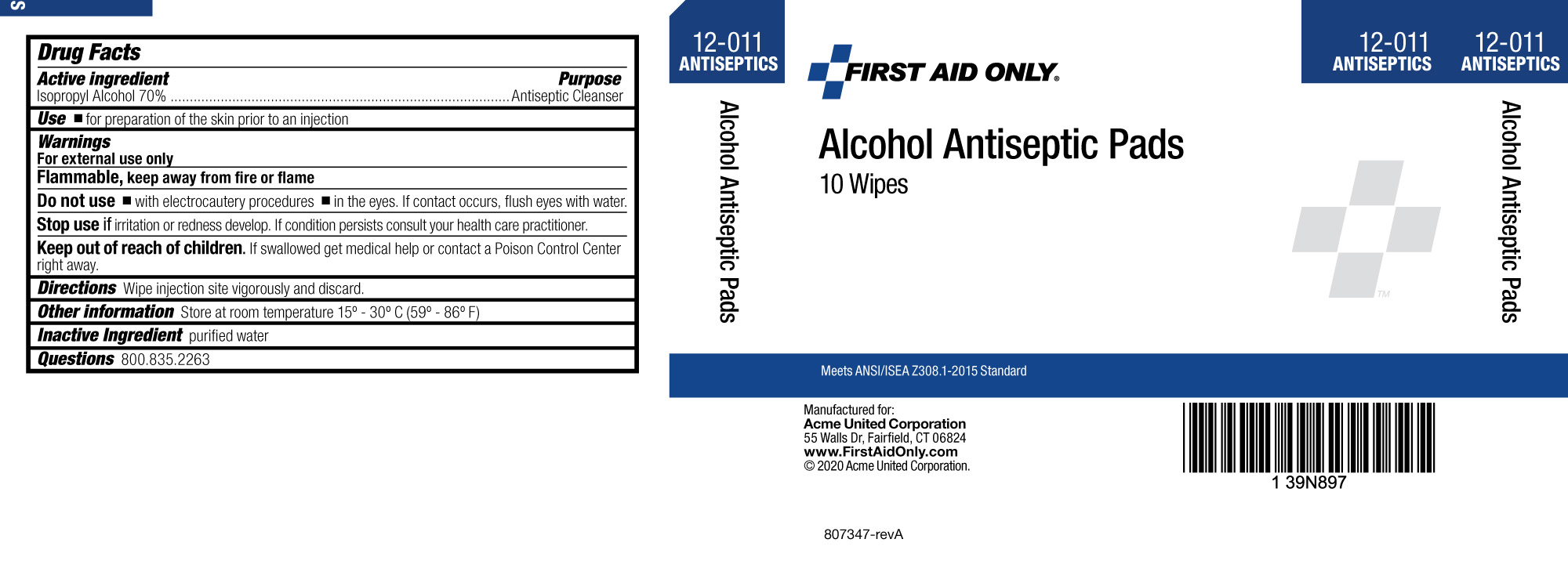 DRUG LABEL: First Aid Only Alcohol Antiseptic Pad
NDC: 0924-0015 | Form: SWAB
Manufacturer: Acme United Coporation
Category: otc | Type: HUMAN OTC DRUG LABEL
Date: 20241123

ACTIVE INGREDIENTS: ISOPROPYL ALCOHOL 0.7 mL/1 mL
INACTIVE INGREDIENTS: WATER

First Aid Only Alcohol Antiseptic Pad

Drug Facts

Active Ingredient

Isopropyl Alcohol, 70%

Purpose

Antiseptic Cleanser

INDICATIONS AND USAGE

Use • for preparation of the skin prior to an injection

WARNINGS

Warnings● For external use only ● Flammable, keep away from fire or flame

Do Not Use ● with electrocautery procedures ● In the eyes. If contact occurs, flush

eyes with water

STOP USE

Slop Use If irritation and redness develop. If condition persists consult your health care practitioner.

Keep out of reach of children. If swallowed, get medical help or consult a Poison

Control Center right away.

DOSAGE AND ADMINISTRATION

Directions Wipe injection site vigorously and discard

Other Information Store at room temperature 15ο - 30ο C (59ο - 86ο F)

Inactive Ingredient purified water